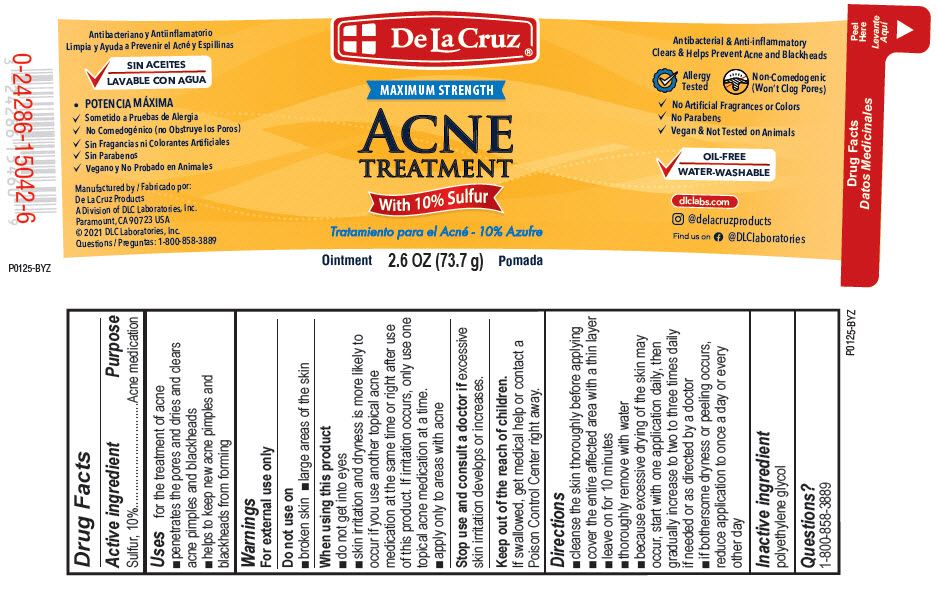 DRUG LABEL: Acne Treatment with Sulfur
NDC: 24286-1574 | Form: OINTMENT
Manufacturer: DLC Laboratories, Inc.
Category: otc | Type: HUMAN OTC DRUG LABEL
Date: 20260107

ACTIVE INGREDIENTS: SULFUR 10 g/100 g
INACTIVE INGREDIENTS: POLYETHYLENE GLYCOL, UNSPECIFIED

Acne Treatment 10% Sulfur

Drug Facts

Active ingredient

Sulfur, 10%

Purpose

Acne medication

Uses

for the treatment of acne

- penetrates the pores and dries and clears acne pimples and blackheads
- helps to keep new acne pimples and blackheads from forming

Warnings

For external use only

Do not use on

- broken skin
- large areas of the skin

When using this product

- do not get into eyes
- skin irritation and dryness is more likely to occur if you use another topical acne medication at the same time or right after use of this product. If irritation occurs, only use one topical acne medication at a time.
- apply only to areas with acne

Stop use and consult a doctor if excessive skin irritation develops or increases.

Keep out of the reach of children.

If swallowed, get medical help or contact a Poison Control Center right away.

Directions

- cleanse the skin thoroughly before applying
- cover the entire affected area with a thin layer
- leave on for 10 minutes
- thoroughly remove with water
- because excessive drying of the skin may occur, start with one application daily, then gradually increase to two to three times daily if needed or as directed by a doctor
- if bothersome dryness or peeling occurs, reduce application to once a day or every other day

Inactive ingredient

polyethylene glycol

Questions

1-800-858-3889

Manufactured by: De La Cruz Products
A Division of DLC Laboratories, Inc.
Paramount, CA 90723 USA

PRINCIPAL DISPLAY PANEL - 73.7 g Jar Label

De La Cruz®

MAXIMUM STRENGTH

ACNE
TREATMENT

With 10% Sulfur

Ointment
2.6 OZ (73.7 g)